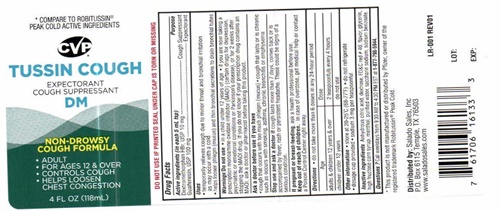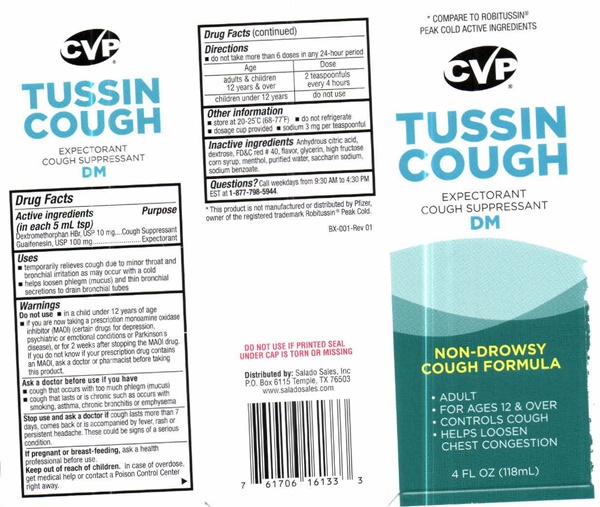 DRUG LABEL: TUSSIN COUGH
NDC: 57243-503 | Form: LIQUID
Manufacturer: Salado Sales, Inc.
Category: otc | Type: HUMAN OTC DRUG LABEL
Date: 20231229

ACTIVE INGREDIENTS: DEXTROMETHORPHAN HYDROBROMIDE 10 mg/5 mL; GUAIFENESIN 100 mg/5 mL
INACTIVE INGREDIENTS: ANHYDROUS CITRIC ACID; DEXTROSE; FD&C RED NO. 40; GLYCERIN; HIGH FRUCTOSE CORN SYRUP; MENTHOL; WATER; SACCHARIN SODIUM; SODIUM BENZOATE

Tussin Cough DM 503

Drug FactsActive ingredients (in each 5 mL tsp)

Dextromethorphan HBr, USP 10 mg
Guaifenesin, USP 100 mg

Purpose

Cough Suppressant
Expectorant

Keep out of reach of children.

In case of overdose, get medical help or contact a Poison Control Center right away

Uses

- temporarily relieves cough due to minor throat and bronchial irritation as may occur with a cold
- helps loosen phlegm (mucus) and thin bronchial secretions to drain bronchial tubes

Warnings

Do not use

- in a child under 12 years of age
- if you are now taking a prescription monoamine oxidase inhibitor (MAOI) (certain drugs for depression, psychiatric or emotional conditions or Parkinson's disease), or for 2 weeks after stopping the MAOI drug. If you do not know if your prescription drug contains an MAOI, ask a doctor or pharmacist before taking this product

Ask A Doctor Before You Use if You Have

- cough that occurs with too much phlegm (mucus)
- cough that lasts or is chronic such as occurs with smoking, asthma, chronic bronchitis, or emphysema

Stop Use And Ask A Doctor If

cough lasts more than 7 days, comes back or is accompanied by fever, rash or persistent headache. These could be signs of a serious condition.

If Pregnant Or Breast-Feeding

ask a health professional before use.

Directions

- do not take more than 6 doses in any 24-hour period

Age Dose

adults & children 2 teaspoonfuls
12 years and over every 4 hours

children under 12 years do not use

Other information

- store at 20-25° C (66-77° F)
- do not refrigerate
- dosage cup provided
- sodium 3 mg per teaspoon

Inactive ingredients

Anhydrous citric acid, dextrose, FD & C red # 40, flavor, glycerin, high fructose corn syrup, menthol, purified water, saccharin sodium, sodium benzoate

Questions?

Call weekdays from 9:30 AM to 4:30 PM EST at

1-877-798-5944

Tussin Cough DM product label

* COMPARE TO ROBITUSSIN® PEAK COLD ACTIVE INGREDIENTS

CVP® CONSUMER VALUE PRODUCTS
TUSSIN COUGH EXPECTORANT COUGH SUPPRESSANT DM

NON-DROWSY COUGH FORMULA

- ADULT
- FOR AGES 12 AND OVER
- CONTROLS COUGH
- HELPS LOOSEN CHEST CONGESTION

4 FL OZ (118 Ml)

* This product is not manufactured or distributed by Pfizer, owner of the registered trademark Robitussin® Peak Cold

Box-001 Rev 01

DO NOT USE IF PRINTED SEAL UNDER CAP IS TORN OR MISSING
Distributed by: Salado Sales, Inc. P.O. Box 6115 Temple, TX 76503 www.saladosales.com

LOT.

EXP.

res